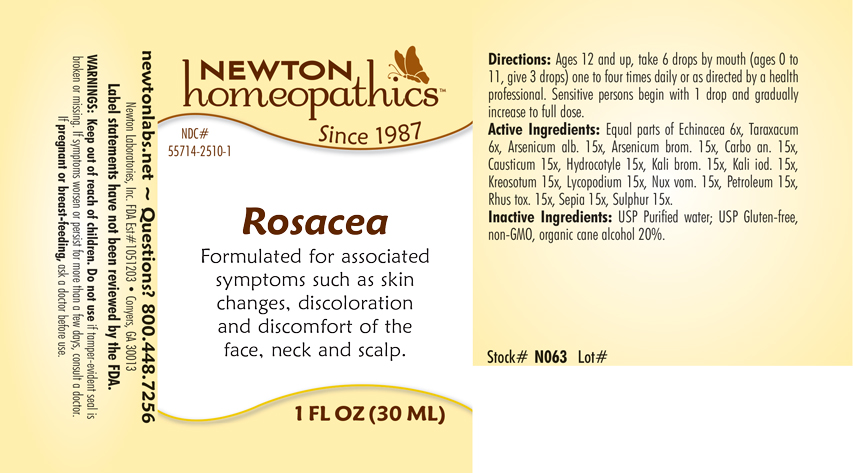 DRUG LABEL: Rosacea
NDC: 55714-2510 | Form: LIQUID
Manufacturer: Newton Laboratories, Inc.
Category: homeopathic | Type: HUMAN OTC DRUG LABEL
Date: 20250210

ACTIVE INGREDIENTS: ECHINACEA, UNSPECIFIED 6 [hp_X]/1 mL; ARSENIC TRIOXIDE 15 [hp_X]/1 mL; ARSENIC TRIBROMIDE 15 [hp_X]/1 mL; CARBO ANIMALIS 15 [hp_X]/1 mL; CAUSTICUM 15 [hp_X]/1 mL; CENTELLA ASIATICA 15 [hp_X]/1 mL; POTASSIUM BROMIDE 15 [hp_X]/1 mL; POTASSIUM IODIDE 15 [hp_X]/1 mL; WOOD CREOSOTE 15 [hp_X]/1 mL; LYCOPODIUM CLAVATUM SPORE 15 [hp_X]/1 mL; STRYCHNOS NUX-VOMICA SEED 15 [hp_X]/1 mL; KEROSENE 15 [hp_X]/1 mL; TOXICODENDRON PUBESCENS LEAF 15 [hp_X]/1 mL; SEPIA OFFICINALIS JUICE 15 [hp_X]/1 mL; SULFUR 15 [hp_X]/1 mL; TARAXACUM OFFICINALE 6 [hp_X]/1 mL
INACTIVE INGREDIENTS: ALCOHOL; WATER

Rosacea 2510L

INDICATIONS & USAGE SECTION

Formulated for associated symptoms such as skin changes, discoloration and disomfort of the face, neck and scalp.

DOSAGE & ADMINISTRATION SECTION

Directions: Ages 12 and up, take 6 drops by mouth (ages 0 to 11, give 3 drops) one to four times daily or as directed by a health professional. Sensitive persons begin with 1 drop and gradually increase to full dose.

OTC - ACTIVE INGREDIENT SECTION

Equal parts of Echinacea 6x, Taraxacum officinale 6x, Arsenicum album 15x, Arsenicum bromatum 15x, Carbo animalis 15x, Causticum 15x, Hydrocotyle asiatica 15x, Kali bromatum 15x, Kali iodatum 15x, Kreosotum 15x, Lycopodium clavatum 15x, Nux vomica 15x, Petroleum 15x, Rhus toxicodendron 15x, Sepia 15x, Sulphur 15x.

OTC - PURPOSE SECTION

Formulated for associated symptoms such as skin changes, discoloration and discomfort of the face, neck and scalp.

INACTIVE INGREDIENT SECTION

Inactive Ingredients: USP Purified Water; USP Gluten-free, non-GMO, organic cane alcohol 20%.

QUESTIONS SECTION

newtonlabs.net – Questions? 800.448.7256

Newton Laboratories, Inc. FDA Est # 1051203 - Conyers, GA 30013

OTC - PREGNANCY OR BREAST FEEDING SECTION

If pregnant or breast-feeding, ask a doctor before use.

WARNINGS SECTION

WARNINGS: Keep out of reach of children. Do not use if tamper-evident seal is broken or missing. If symptoms worsen or persist for more than a few days, consult a doctor. If pregnant or breast-feeding, ask a doctor before use.

OTC - KEEP OUT OF REACH OF CHILDREN SECTION

Keep out of reach of children.